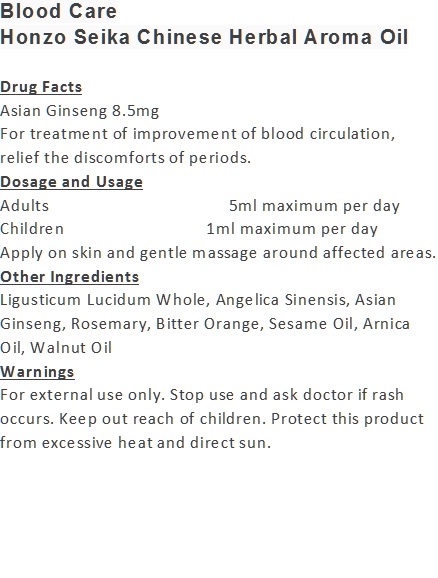 DRUG LABEL: Blood Care
NDC: 71263-9903 | Form: OIL
Manufacturer: NIC CO., LTD.
Category: otc | Type: HUMAN OTC DRUG LABEL
Date: 20170101

ACTIVE INGREDIENTS: ASIAN GINSENG 8.5 mg/100 mL; ANGELICA SINENSIS ROOT 3 mg/100 mL
INACTIVE INGREDIENTS: ARNICA MONTANA; SESAME OIL; LIGUSTICUM LUCIDUM WHOLE; WALNUT OIL; ROSEMARY OIL; BITTER ORANGE OIL

Drug Facts

Asian Ginseng 8.5mg

Use

For treatment of improvement of blood circulation, relief the discomforts of periods.

Dosage Suggestion

Adults 5ml maximum per day

Children 1ml maximum per day

INACTIVE INGREDIENT

Other Ingredients

Ligusticum Lucidum Whole, Angelica Sinensis, Rosemary, Bitter Orange, Sesame Oil, Arnica Oil, Walnut Oil

Directions

Apply on skin and gentle massage around affected area.

Warnings

For external use only. Stop use and ask doctor if rash occurs. Keep out reach of children.

Other Information

Protect this product from excessive heat

and direct sun.

Warnings

For external use only. Stop use and ask doctor if rash occurs. Keep out reach of children.